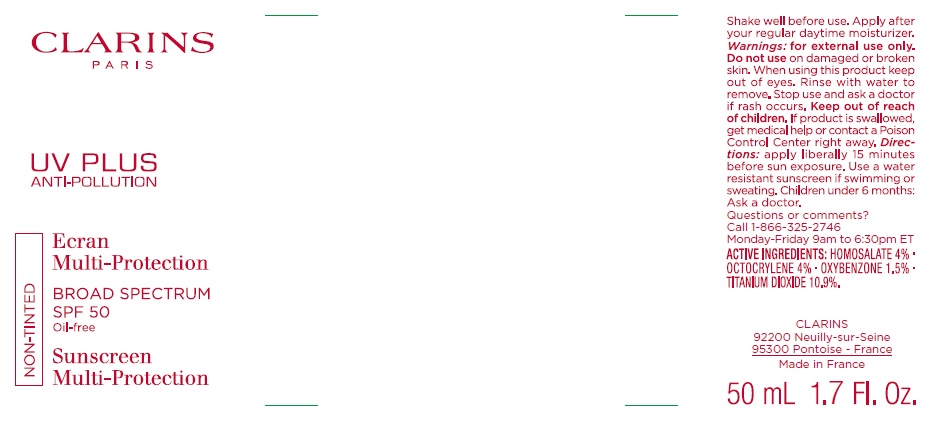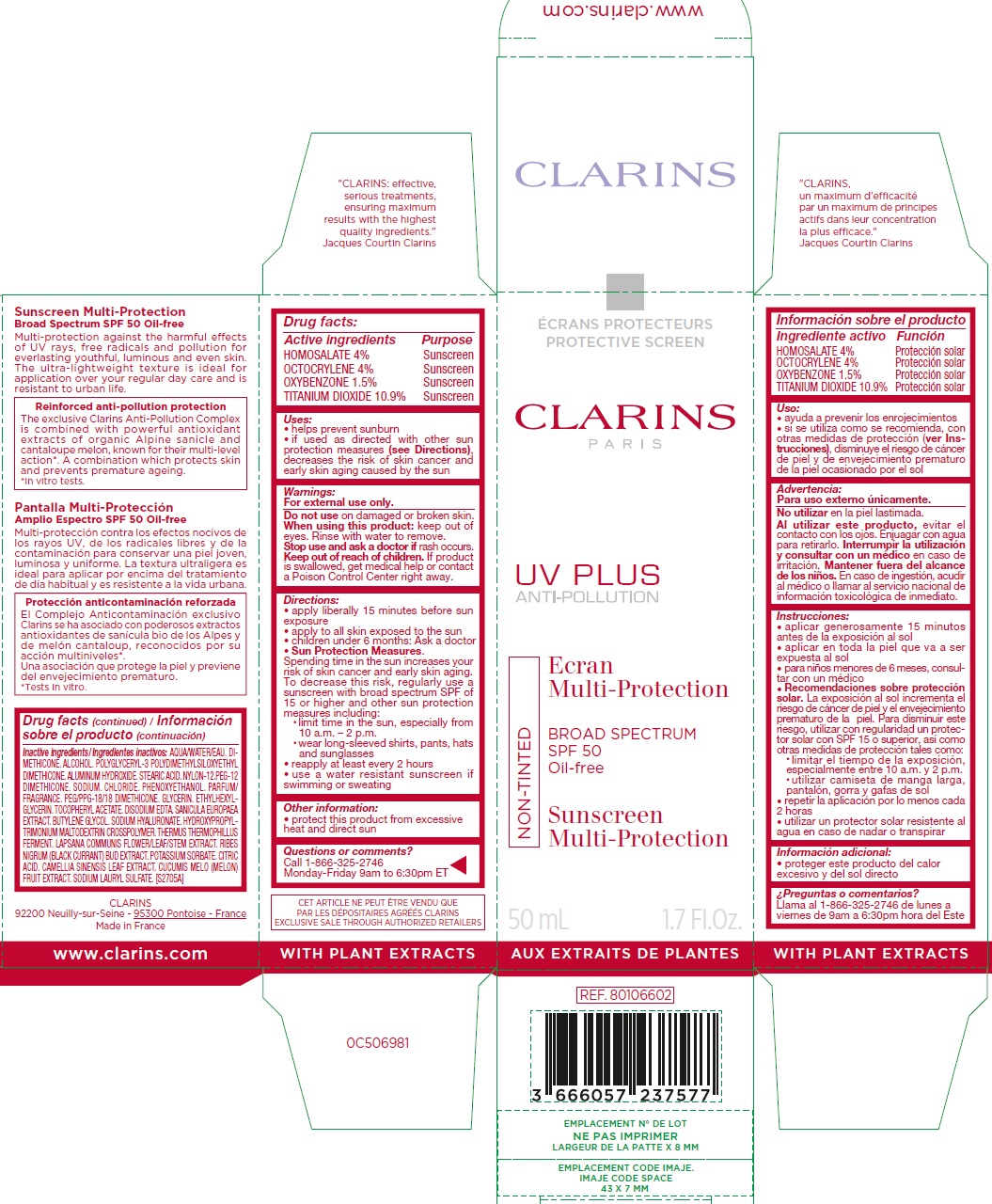 DRUG LABEL: CLARINS UV PLUS ANTI-POLLUTION BROAD SPECTRUM SPF 50 NON-TINTED Sunscreen Multi-Protection
NDC: 58668-2951 | Form: LIQUID
Manufacturer: Laboratoires Clarins
Category: otc | Type: HUMAN OTC DRUG LABEL
Date: 20231011

ACTIVE INGREDIENTS: HOMOSALATE 40 mg/1 mL; OCTOCRYLENE 40 mg/1 mL; OXYBENZONE 15 mg/1 mL; TITANIUM DIOXIDE 109 mg/1 mL
INACTIVE INGREDIENTS: WATER; DIMETHICONE; ALCOHOL; ALUMINUM HYDROXIDE; STEARIC ACID; NYLON-12; PEG-12 DIMETHICONE (300 CST); SODIUM CHLORIDE; PHENOXYETHANOL; PEG/PPG-18/18 DIMETHICONE; GLYCERIN; ETHYLHEXYLGLYCERIN; .ALPHA.-TOCOPHEROL ACETATE; EDETATE DISODIUM; BUTYLENE GLYCOL; HYALURONATE SODIUM; THERMUS THERMOPHILUS LYSATE; LAPSANA COMMUNIS FLOWERING TOP; RIBES NIGRUM FLOWER BUD; POTASSIUM SORBATE; CITRIC ACID MONOHYDRATE; GREEN TEA LEAF; MUSKMELON; SODIUM LAURYL SULFATE

CLARINS UV PLUS ANTI-POLLUTION BROAD SPECTRUM SPF 50 OIL-FREE NON-TINTED Sunscreen Multi-Protection

Active Ingredient

HOMOSALATE 4%
OCTOCRYLENE 4%
OXYBENZONE 1.5%
TITANIUM DIOXIDE 10.9%

Purpose

Sunscreen

Uses:

- helps prevent sunburn
- if used as directed with other sun protection measures (see Directions), decreases the risk of skin cancer and early skin aging caused by the sun

Warnings:

For external use only.

Do not use

On damaged or broken skin.

When using this product:

keep out of eyes. Rinse with water to remove.

Stop use and ask a doctor if

rash occurs.

Keep out of reach of children.

If product is swallowed, get medical help or contact a Poison Control Center right away.

Directions:

- apply liberally 15 minutes before sun exposure
- Apply to all skin exposed to the sun
- children under 6 months: Ask a doctor
- Sun Protection Measures. Spending time in the sun increases your risk of skin cancer and early skin aging. To decrease this risk, regularly use a sunscreen with broad spectrum SPF of 15 or higher and other sun protection measures including:
-
  - limit time in the sun, especially from 10 a.m. – 2 p.m.
  - wear long-sleeved shirts, pants, hats and sunglasses
- reapply at least every 2 hours
- use a water resistant sunscreen if swimming or sweating

Other information:

- protect this product from excessive heat and direct sun

Questions or comments?

Call 1-866-325-2746 Monday-Friday 9am to 6:30pm ET

Inactive ingredients

AQUA/WATER/EAU. DIMETHICONE. ALCOHOL. POLYGLYCERYL-3 POLYDIMETHYLSILOXYETHYL DIMETHICONE. ALUMINUM HYDROXIDE. STEARIC ACID. NYLON-12.PEG-12 DIMETHICONE. SODIUM. CHLORIDE. PHENOXYETHANOL. PARFUM/ FRAGRANCE. PEG/PPG-18/18 DIMETHICONE. GLYCERIN. ETHYLHEXYLGLYCERIN. TOCOPHERYL ACETATE. DISODIUM EDTA. SANICULA EUROPAEA EXTRACT. BUTYLENE GLYCOL. SODIUM HYALURONATE. HYDROXYPROPYLTRIMONIUM MALTODEXTRIN CROSSPOLYMER. THERMUS THERMOPHILLUS FERMENT. LAPSANA COMMUNIS FLOWER/LEAF/STEM EXTRACT. RIBES NIGRUM (BLACK CURRANT) BUD EXTRACT. POTASSIUM SORBATE. CITRIC ACID. CAMELLIA SINENSIS LEAF EXTRACT. CUCUMIS MELO (MELON) FRUIT EXTRACT. SODIUM LAURYL SULFATE. [S2705A]